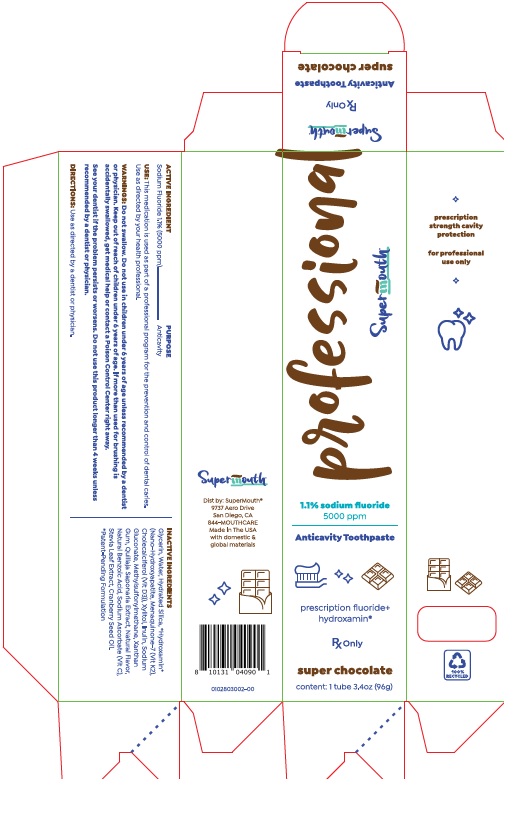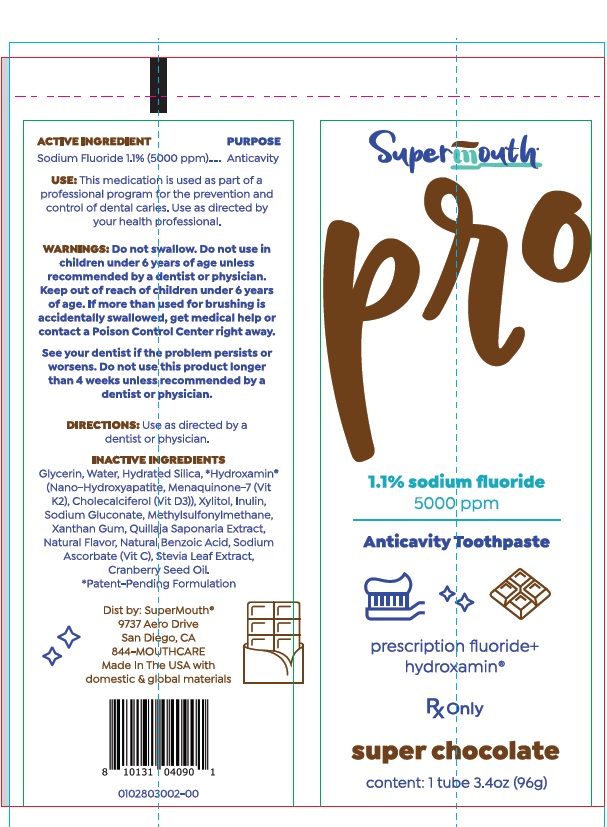 DRUG LABEL: Super Chocolate Prescription
NDC: 83729-103 | Form: PASTE, DENTIFRICE
Manufacturer: SuperMouth, LLC.
Category: prescription | Type: Human Prescription Drug Label
Date: 20251112

ACTIVE INGREDIENTS: SODIUM FLUORIDE 1.1 g/100 g
INACTIVE INGREDIENTS: GLYCERIN; WATER; HYDRATED SILICA; TRIBASIC CALCIUM PHOSPHATE; MENAQUINONE 7; CHOLECALCIFEROL; XYLITOL; INULIN; SODIUM GLUCONATE; DIMETHYL SULFONE; XANTHAN GUM; QUILLAJA SAPONARIA WHOLE; BENZOIC ACID; SODIUM ASCORBATE; STEVIA LEAF; CRANBERRY SEED OIL

SuperMouth Super Chocolate Prescription Toothpaste

ACTIVE INGREDIENT
Sodium Fluoride 1.1% (5000 ppm)

PURPOSE
Sodium Fluoride …. Anticavity

INACTIVE INGREDIENT

USE: This medication is used as part of a professional program for the prevention and control of dental caries. Use as directed by your health professional.

WARNINGS AND PRECAUTIONS

WARNINGS: Do not swallow. Do not use in children under 6 years of age unless recommended by a dentist or physician. Keep out of reach of children under 6 years of age. If more than used for brushing is accidentally swallowed, get medical help or contact a Poison Control Center right away.

See your dentist if the problem persists or worsens. Do not use this product longer than 4 weeks unless recommended by a dentist or physician.

DOSAGE AND ADMINISTRATION

DIRECTIONS: Use as directed by a dentist or physician.

INACTIVE INGREDIENTS

Glycerin, Water, Hydrated Silica, *Hydroxamin® (Nano-Hydroxyapatite, Menquinone-y (Vit K2), Cholecalciferol (Vit D3)), Xylitol, Inulin, Sodium Gluconate, Methylsulfonylmethane, Xanthan Gum, Quillaja Saponaria Extract, Natural Flavor, Natural Benzoic Acid, Sodium Ascorbate (Vit C), Stevia Leaf Extract, Cranberry Seed Oil.
*Patent-Pending Formulation

PRINCIPAL DISPLAY PANEL - SuperMouth Super Chocolate Prescription Toothpaste

Supermouth Pro

1.1% sodium fluoride

5000 ppm

Anticavity Toothpaste

Rx Only

super chocolate

content: 1 tube 3.4oz (96g)

Dist by: SuperMouth®
9737 Aero Drive
San Diego, CA
844-MOUTHCARE
Made In The USA with
Domestic & global materials

res